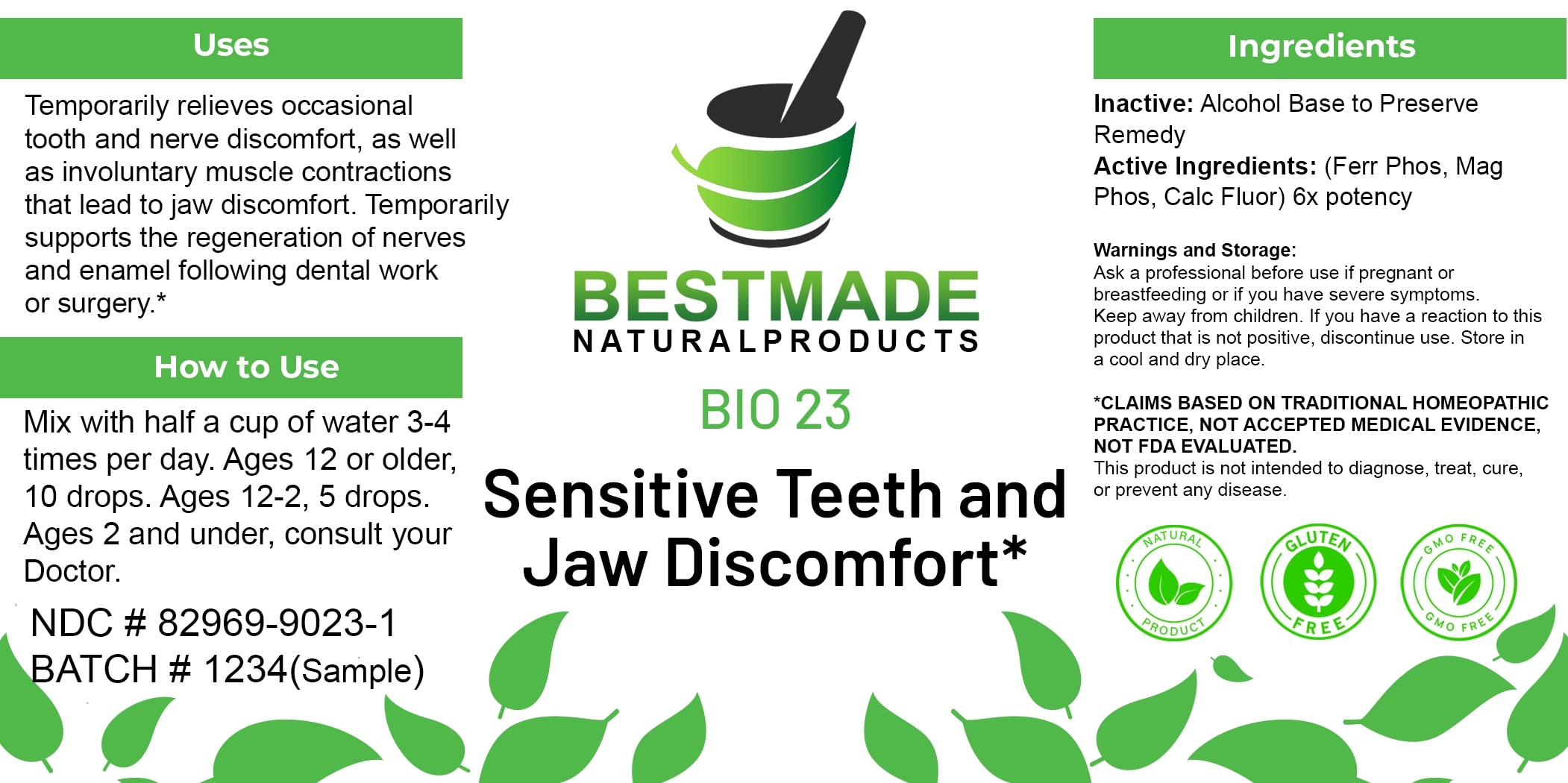 DRUG LABEL: Bestmade Natural Products BIO23
NDC: 82969-9023 | Form: LIQUID
Manufacturer: Bestmade Natural Products
Category: homeopathic | Type: HUMAN OTC DRUG LABEL
Date: 20250311

ACTIVE INGREDIENTS: FERROSOFERRIC PHOSPHATE 6 [hp_X]/6 [hp_X]; CALCIUM FLUORIDE 6 [hp_X]/6 [hp_X]; MAGNESIUM PHOSPHATE, DIBASIC TRIHYDRATE 6 [hp_X]/6 [hp_X]
INACTIVE INGREDIENTS: ALCOHOL 6 [hp_X]/6 [hp_X]

BIO 23 Sensitive Teeth and Jaw Discomfort*

DOSAGE AND ADMINISTRATION

How to Use

Mix with half a cup of water 3-4 times per day. Ages 12 or older, 10 drops. Ages 12-2, 5 drops. Ages 2 and under, consult your Doctor.

Inactive:

Alcohol Base to Preserve Product

Active Ingredients:

(Ferr Phos, Mag Phos, Calc Fluor) 6x potency

Uses

Temporarily relieves occasional tooth and nerve discomfort. as well as involuntarv muscle contractions that lead to jaw discomfort. Temporarily supports the regeneration of nerves and enamel following dental work or surgery.*

*CLAIMS BASED ON TRADITIONAL HOMEOPATHIC PRACTICE, NOT ACCEPTED MEDICAL EVIDENCE, NOT FDA EVALUATED.

This product is not intended to diagnose, treat, cure, or prevent any disease.

Uses

Temporarily relieves occasional tooth and nerve discomfort. as well as involuntarv muscle contractions that lead to jaw discomfort. Temporarily supports the regeneration of nerves and enamel following dental work or surgery.*

*CLAIMS BASED ON TRADITIONAL HOMEOPATHIC PRACTICE, NOT ACCEPTED MEDICAL EVIDENCE, NOT FDA EVALUATED.

This product is not intended to diagnose, treat, cure, or prevent any disease.

KEEP OUT OF REACH OF CHILDREN

Warnings and Storage:

Ask a professional before use if pregnant or breastfeeding or if you have severe symptoms. Keep away from children. If you have a reaction to this product that is not positive, discontinue use. Store in a cool and dry place.

Warnings and Storage:

Ask a professional before use if pregnant or breastfeeding or if you have severe symptoms. Keep away from children. If you have a reaction to this product that is not positive, discontinue use. Store in a cool and dry place.

*CLAIMS BASED ON TRADITIONAL HOMEOPATHIC PRACTICE, NOT ACCEPTED MEDICAL EVIDENCE NOT FDA EVALUATED.

This product is not intended to diagnose, treat, cure, or prevent any disease.

Entire package label